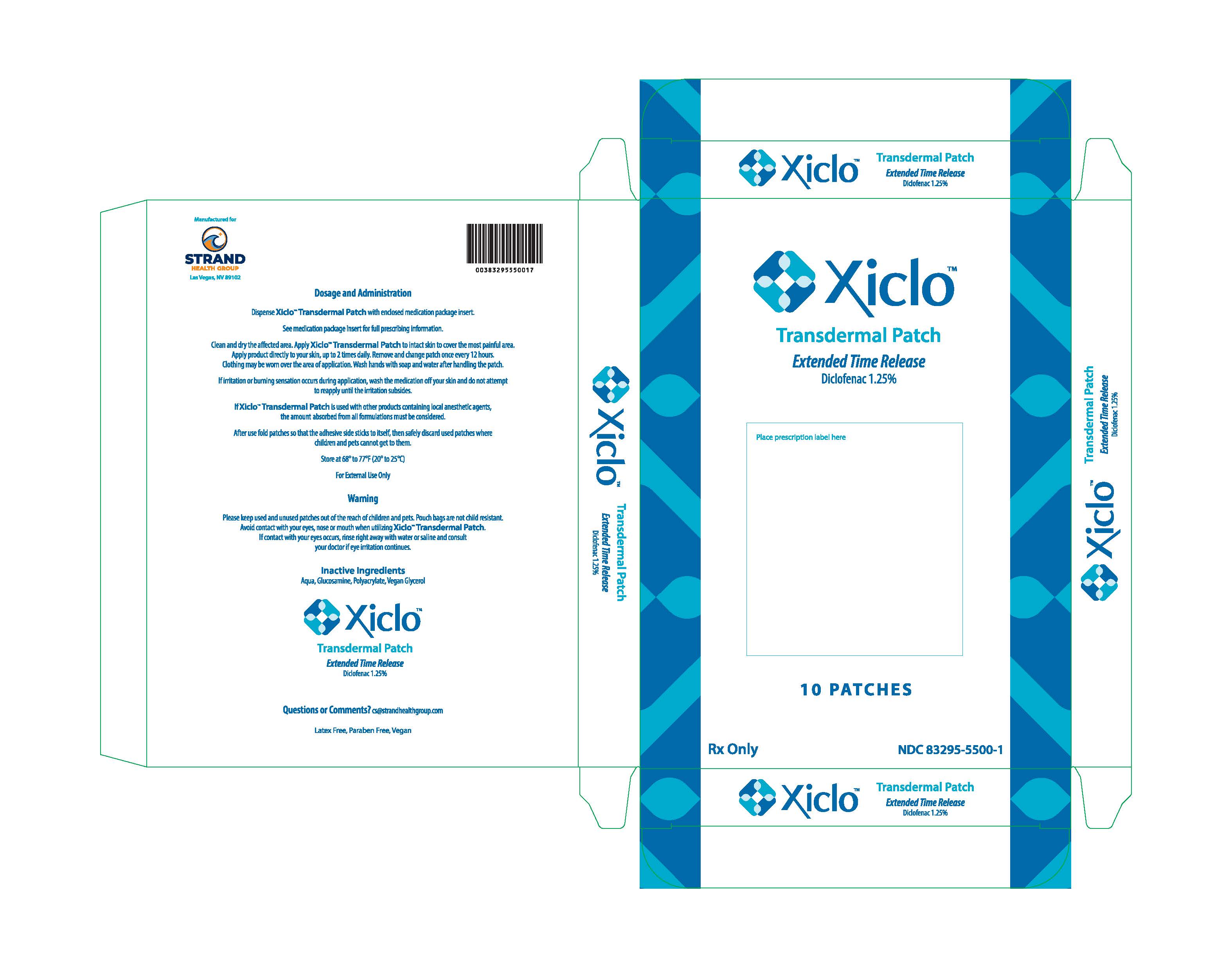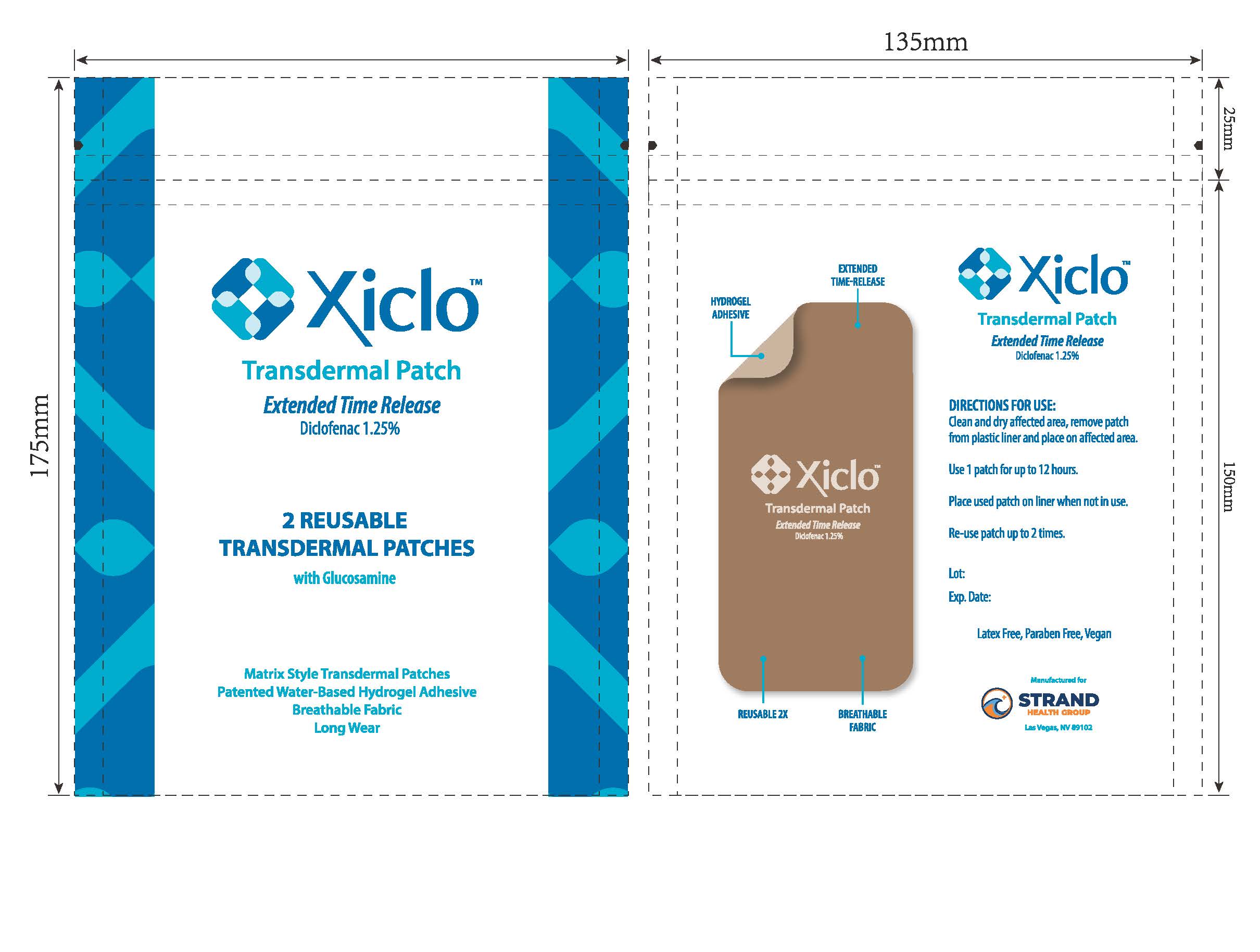 DRUG LABEL: Xiclo
NDC: 83295-5500 | Form: PATCH
Manufacturer: Strand Health Group
Category: prescription | Type: HUMAN PRESCRIPTION DRUG LABEL
Date: 20251218

ACTIVE INGREDIENTS: DICLOFENAC 0.0125 g/1 g
INACTIVE INGREDIENTS: GLUCOSAMINE; POLYACRYLATE-13; GLYCERIN

Xiclo Patch

Xiclo™ Transdermal Patch

Diclofenac 1.25%

Rx Only

1. Indications and Usage

2. Dosage and Administration

2.1 General Dosing Instructions

2.2 Dosing and Instructions for Use

3. Dosage Forms and Strengths

4. Contraindications

5. Warnings, Precautions, and Adverse Reactions

5.1 Risk of Serious Cardiovascular and Gastrointestinal Events

5.2 Gastrointestinal Bleeding, Ulceration, and Perforation

5.3 Hepatotoxicity

5.4 Renal Toxicity and Hyperkalemia

5.5 Anaphylactic Reactions

5.6 Exacerbation of Asthma Related to Aspirin Sensitivity

5.7 Serious Skin Reactions

5.8 Hematologic Toxicity

5.9 Masking of Inflammation and Fever

5.10 Sun Exposure

5.11 Excessive Dosing

5.12 Application-Associated Pain

5.13 Increase in Blood Pressure

5.14 Sensory Function

5.15 Precautions

5.16 Other Adverse Events

5.17 Systemic (Dose-Related) Reactions

5.18 Oral Nonsteroidal Anti-Inflammatory Drugs

6. Drug Interactions

7. Use in Specific Populations

7.1 Pregnancy

7.2 Lactation

7.3 Pediatric Use

7.4 Geriatric Use

8. Overdosage

9. Description

10. Clinical Pharmacology

10.1 Mechanism of Action

10.2 Pharmacokinetics

11. Nonclinical Toxicology

11.1 Carcinogenesis, Mutagenesis, Impairment of Fertility

12. How Supplied / Storage and Handling

12.1 How Supplied

12.2 Storage

12.3 Handling and Disposal

13. Patient Counseling Information

14. General Information on NSAIDs

1. INDICATIONS & USAGE

Xiclo™ Transdermal Patch is indicated in adults over the age of 12 years old for the treatment of signs and symptoms of osteoarthritis of the joints, and of acute and chronic pain in muscles and joints associated with muscle soreness, strains, sprains, arthritis, simple backache, muscle stiffness, and more.

2. DOSAGE & ADMINISTRATION

2.1 General Dosing Instructions

- Use Xiclo™ Transdermal Patch only on dry, intact (unbroken) skin.
- Use the lowest effective dosage for the shortest duration consistent with individual patient treatment goals.
- Avoid contact with eyes and mucous membranes.
- Avoid concomitant use of Xiclo™ Transdermal Patch on the treated skin site with other external products, including sunscreens, cosmetics, lotions, moisturizers, insect repellants, or other external medications.
- Do not use combination therapy with diclofenac and an oral NSAID unless the benefit outweighs the risk and conduct periodic assessments.

2.2 Dosing and Instructions for Use

- Tear open pouch bag and remove one patch. Place remaining patches back in pouch bag and seal pouch bag closed.
- Peel the clear plastic film away and apply Xiclo™ Transdermal Patch to intact skin to cover most painful area. Apply one patch per day for up to 12 hours within a 24-hout period (12 on, 12 off). One single Xiclo™ Transdermal Patch may be used twice per day. To re-use after the first application, place the clear plastic film back onto the medicated hydrogel pad.

3. DOSAGE FORMS & STRENGTHS

Xiclo™ Transdermal Patch contains 1.25% diclofenac. Each patch is 2 in x 4 in (5.08 cm x 10.16 cm) and consists of an adhesive side containing active/inactive ingredients and an outer surface backing layer. The adhesive side is covered with a removable, clear, plastic film. The outer surface of the backing layer is imprinted with the Xiclo™ Transdermal Patch logo.

4. CONTRAINDICATIONS

Xiclo™ Transdermal Patch is contraindicated in patients with a known history of hypersensitivity to non-steroidal anti-inflammatory medications such as diclofenac. Diclofenac is contraindicated in the setting of coronary artery bypass graft (CABG) surgery. History of asthma, uticaria, or allergic-type reactions after absorbing non-steroidal anti-inflammatory drugs (NSAIDs) should also be considered.

5. WARNINGS, PRECAUTIONS & ADVERSE REACTIONS

5.1 Risk of Serious Cardiovascular and Gastrointestinal Events

Nonsteroidal anti-inflammatory drugs (NSAIDs) can cause an increased risk of serious cardiovascular (CV) thrombotic events, including myocardial infarction and stroke, which can be fatal. This risk may occur early in treatment and may increase with duration of use. NSAIDs, including diclofenac, can lead to new onset of hypertension, or worsening of preexisting hypertension, either of which may contribute to the increased incidence of CV events. To minimize the potential risk for an adverse CV event in NSAID-treated patients, use the lowest effective dose for the shortest duration possible. Avoid the use of diclofenac external in patients with a recent MI unless the benefits are expected to outweigh the risk of recurrent CV thrombotic events. If diclofenac external is used in patients with a recent MI, monitor patients for signs of cardiac ischemia. Avoid using NSAIDs within 14 days following coronary artery bypass graft (CABG) surgery.

5.2 Gastrointestinal Bleeding, Ulceration, and Perforation

Nonsteroidal anti-inflammatory drugs (NSAIDs) can cause an increased risk of serious gastrointestinal (GI) adverse events including bleeding, ulceration, and perforation of the stomach or intestines, which can be fatal. These events can occur at any time during use and without warning symptoms. Other factors that increase the risk of GI bleeding in patients treated with NSAIDs include concomitant use of oral corticosteroids, aspirin, anticoagulants, or selective serotonin reuptake inhibitors (SSRIs). Elderly patients and patients with a prior history of peptic ulcer disease and/or GI bleeding are at greater risk for serious GI events. Additionally, patients with advanced liver disease and/or coagulopathy are at increased risk for GI bleeding.

5.3 Hepatotoxicity

In postmarketing reports, cases of drug-induced hepatotoxicity have been reported in the first month, and in some cases, the first 2 months of therapy, but can occur at any time during treatment with diclofenac. Postmarketing surveillance has reported cases of severe hepatic reactions, including liver necrosis, jaundice, fulminant hepatitis, with and without jaundice, and liver failure. Some of these reported cases resulted in fatalities or liver transplantation. Monitor for 4 to 8 weeks after initiating treatment with diclofenac. However, severe hepatic reactions can occur at any time during treatment with diclofenac. Inform patients of the warning signs and symptoms of hepatotoxicity (e.g., nausea, fatigue, lethargy, diarrhea, pruritus, jaundice, right upper quadrant tenderness, and “flu-like” symptoms). To minimize potential risk for an adverse liver-related event in patients treated with diclofenac external, exercise caution when prescribing diclofenac external with concomitant drugs that are known to be potentially hepatotoxic (e.g., acetaminophen, antibiotics, antiepileptics).

5.4 Renal Toxicity and Hyperkalemia

Renal Toxicity

Long-term administration of NSAIDs has resulted in renal papillary necrosis and other renal injury. Renal toxicity has also been seen in patients in whom renal prostaglandins have a compensatory role in the maintenance of renal perfusion. In these patients, administration of an NSAID may cause a dose-dependent reduction in prostaglandin formation and, secondarily, in renal blood flow, which may precipitate overt renal decompensation. Patients at greatest risk of this reaction are those with impaired renal function, dehydration, hypovolemia, heart failure, liver dysfunction, those taking diuretics and ACE inhibitors or ARBs, and the elderly. Discontinuation of NSAID therapy was usually followed by recovery to the pretreatment state. Avoid the use of diclofenac external in patients with advanced renal disease unless the benefits are expected to outweigh the risk of worsening renal function. If diclofenac is used in patients with advanced renal disease, monitor patients for signs of worsening symptoms.

Hyperkalemia

Increases in serum potassium concentration, including hyperkalemia, have been reported with use of NSAIDs, even in some patients without renal impairment. In patients with normal renal function, these effects have been attributed to a hyporeninemic-hypoaldosteronism state.

5.5 Anaphylactic Reactions

Diclofenac has been associated with anaphylactic reactions in patients with and without known hypersensitivity to diclofenac and in patients with aspirin-sensitive asthma. Seek emergency help if an anaphylactic reaction occurs.

5.6 Exacerbation of Asthma Related to Aspirin Sensitivity

A subpopulation of patients with asthma may have aspirin-sensitive asthma which may include chronic rhinosinusitis complicated by nasal polyps; severe, potentially fatal bronchospasm; and/or intolerance to aspirin and other NSAIDs. Because cross-reactivity between aspirin and other NSAIDs has been reported in such aspirin-sensitive patients, diclofenac external is contraindicated in patients with this form of aspirin sensitivity. When diclofenac is used in patients with preexisting asthma, monitor patients for changes in the signs and symptoms.

5.7 Serious Skin Reactions

NSAIDs, including diclofenac, can cause serious skin adverse reactions such as exfoliative dermatitis, Stevens-Johnson Syndrome (SJS), and toxic epidermal necrolysis (TEN), which can be fatal. Inform patients about the signs and symptoms of serious skin reactions, and to discontinue the use of diclofenac external at the first appearance of any skin hypersensitivity.

5.8 Hematologic Toxicity

Anemia has occurred in NSAID-treated patients. If a patient treated with diclofenac external has any signs or symptoms of anemia, monitor hemoglobin or hematocrit. NSAIDs, including diclofenac, may increase the risk of bleeding events. Co-morbid conditions such as coagulation disorders, concomitant use of warfarin, other anticoagulants, antiplatelet agents (e.g., aspirin), serotonin reuptake inhibitors (SSRIs) may increase this risk.

5.9 Masking of Inflmmation and Fever

The pharmacological activity of diclofenac in reducing inflammation, and possibly fever, may diminish the utility of diagnostic signs in detecting infections.

5.10 Sun Exposure

Instruct patients to avoid exposure to natural or artificial sunlight after treatment of Xiclo™ Transdermal Patch because studies in animals indicated external diclofenac treatment resulted in an earlier onset of ultraviolet light-induced skin tumors. The potential effects of diclofenac external on skin response to ultraviolet damage in humans are not known.

5.11 Excessive Dosing

Excessive dosing by applying larger amounts of Xiclo™ Transdermal Patch could result in increased absorption of diclofenac and high blood concentrations. Longer duration of application, application of more than the recommended dosage, smaller patients, or impaired elimination may all contribute to increasing the blood concentration of diclofenac.

5.12 Application-Associated Pain

During or immediately after treatment with Xiclo™ Transdermal Patch, the skin at the site of application may develop blisters, bruising, burning sensation, depigmentation, dermatitis, discoloration, edema, erythema, exfoliation, irritation, papules, petechia, pruritus, vesicles, or may be the locus of abnormal sensation. These reactions are generally mild and transient, resolving spontaneously within a few minutes to hours.

5.13 Increase in Blood Pressure

Patient with unstable or poorly controlled hypertension, or a recent history of cardiovascular or cerebrovascular events, may be at increased risk of adverse cardiovascular effects. Consider these factors prior to initiating Xiclo™ Transdermal Patch treatment. Monitor blood pressure periodically during and following the treatment procedure and provide adequate support for treatment-related pain.

5.14 Sensory Function

Decreases in sensory functions are generally minor and temporary (including thermal and other harmful stimuli). All patients with pre-existing sensory deficits should be clinically assessed for signs of sensory deterioration or loss prior to each prescription of Xiclo™ Transdermal Patch. If sensory deterioration or loss is detected or pre-existing sensory deficit worsens, continued use of Xiclo™ Transdermal Patch treatment should be reconsidered.

5.15 Precautions

Allergic Reactions

Xiclo™ Transdermal Patch should be used with caution in patients with a history of drug sensitivities, especially if the etiologic agent is uncertain.

External Heat Sources

Placement of external heat sources, such as heating pads or electric blankets, over Xiclo™ Transdermal Patch is not recommended.

Eye Exposure

The contact of Xiclo™ Transdermal Patch with eyes should be avoided based on finding from previous studies with use of similar products. If eye contact occurs, immediately wash out the eye with water and saline and protect the eye until sensation returns.

Non-Intact Skin

Xiclo™ Transdermal Patch is only recommended for use on intact skin. Application to broken or inflamed skin may result in increased irritation and/or increased absorption of ingredients.

5.16 Other Adverse Events

Due to the nature and limitation of spontaneous reports in postmarketing surveillance, causality has not been established for additional reported adverse events including asthenia, confusion, disorientation, dizziness, headache, hyperesthesia, hypoesthesia, lightheadedness, metallic taste, nausea, nervousness, pain exacerbated, paresthesia, somnolence, taste alteration, vomiting, visual disturbances such as blurred vision, flushing, tinnitus, and tremor.

5.17 Systemic (Dose-Related) Reactions

Systemic adverse reactions following appropriate use of XiclofenTM Transdermal Patch are unlikely due to the small dose absorbed.

5.18 Oral Nonsteroidal Anti-Inflammatory Drugs

Concomitant use of oral NSAIDs with diclofenac external resulted in a higher rate of rectal hemorrhage, more frequent abnormal creatinine, urea, and hemoglobin. Therefore, do not use combination therapy with diclofenac external and an oral NSAID unless the benefit outweighs the risk and conduct periodic laboratory evaluations.

6. DRUG INTERACTIONS

Drugs That Interfere with Hemostasis

Monitor patients with concomitant use of diclofenac external with anticoagulants (e.g., warfarin), antiplatelet agents (e.g., aspirin), selective serotonin reuptake inhibitors (SSRIs), and serotonin norepinephrine reuptake inhibitors (SNRIs) for signs of bleeding.

Aspirin

Concomitant use of diclofenac external and analgesic doses of aspirin is not generally recommended because of the increased risk of bleeding.

ACE Inhibitors, Angiotensin Receptor Blockers, and Beta-Blockers

When these drugs are administered concomitantly, patients should be adequately hydrated. Assess renal function at the beginning of the concomitant treatment.

Diuretics

During concomitant use of diclofenac external with diuretics, observe patients for signs of worsening renal function, in addition to assuring diuretic efficacy including antihypertensive effects.

Digoxin

During concomitant use of diclofenac external and digoxin, monitor serum digoxin levels.

Lithium

During concomitant use of diclofenac external and lithium, monitor patients for signs of lithium toxicity.

Methotrexate

During concomitant use of diclofenac external and methotrexate, monitor patients for methotrexate toxicity.

Cyclosporine

During concomitant use of diclofenac external and cyclosporine, monitor patients for signs of worsening renal function.

Pemetrexed

Concomitant use of diclofenac external and pemetrexed may increase the risk of pemetrexed-associated myelosuppression, renal, and GI toxicity.

7. USE IN SPECIFIC POPULATIONS

7.1 Pregnancy

Diclofenac may cause premature closure of the fetal ductus arteriosus. Avoid use of NSAIDs, including diclofenac external, in pregnant women starting at 30 weeks of gestation. There are no adequate and well-controlled studies of diclofenac external in pregnant women.

7.2 Lactation

Based on available data, diclofenac may be present in human milk. Caution should be exercised when XiclofenTM Transdermal Patch is administered to a nursing woman. The developmental and health benefits of breastfeeding should be considered along with the mother’s clinical need for XiclofenTM Transdermal Patch and any potential adverse effects on the breastfed infant.

7.3 Pediatric Use

Safety and effectiveness in pediatric patients under the age of 12 has not been established.

7.4 Geriatric Use

Elderly patients, compared to younger patients, are at a greater risk of NSAID-associated serious cardiovascular, gastrointestinal, and/or renal adverse reactions. If a risk is present, start dosing at the low end of the dosing range, and monitor patients for adverse effects.

8. OVERDOSAGE

Symptoms following acute NSAID overdosages have been typically limited to lethargy, drowsiness, nausea, vomiting, and epigastric pain, which have been generally reversible with supportive care. Gastrointestinal bleeding has occurred. Hypertension, acute renal failure, respiratory depression, and coma have occurred, but were rare. Manage patients with symptomatic and supportive care following an NSAID overdosage. There are no specific antidotes. For additional information about overdose treatment, contact your poison control center.

9. DESCRIPTION

Xiclo™ Transdermal Patch is comprised of an adhesive material containing 1.25% diclofenac. Each patch is 2 in x 4 in (5.06 cm x 10.16 cm) and consists of an adhesive side containing the active/inactive ingredients and an outer surface backing layer with breathable fabric. The adhesive side is covered with a removable, clear, unprinted, plastic film. The outer surface of the backing layer is imprinted with the Xiclo™ Transdermal Patch logo. 2 patches are in each pouch bag. The inactive ingredients include: Glucosamine, Polyacrylate, Vegan Glycerol, and Water. Xiclo™ Transdermal Patch is Latex Free, Paraben Free, and Vegan.

10. CLINICAL PHARMACOLOGY

10.1 Mechanism of Action

Diclofenac has analgesic, anti-inflammatory, and antipyretic properties. The mechanism of action of diclofenac, like that of other NSAIDs, is not completely understood but involves inhibition of cyclooxygenase (COX-1 and COX-2). Diclofenac is a potent inhibitor of prostaglandin synthesis in vitro. Diclofenac concentrations reached during therapy have produced in vivo effects. Prostaglandins sensitive afferent nerves and potentiate the action of bradykinin in inducing pain in animal models. Prostaglandins are mediators of inflammation. Because diclofenac is an inhibitor of prostaglandin synthesis, its mode of action may be due to a decrease of prostaglandins in peripheral tissues.

10.2 Pharmacokinetics

Diclofenac is more than 99% bound to human serum proteins, primarily to albumin. Diclofenac diffuses into and out of the synovial fluid. Diffusion into the joint occurs when plasma levels are higher than those in the synovial fluid, after which the process reverses and synovial fluid levels are higher than plasma levels. It is not known whether diffusion into the joint plays a role in the effectiveness of diclofenac. Five diclofenac metabolites have been identified in human plasma and urine. The metabolites include 4’-hydroxy-, 5-hydroxy-, 3/hydroxy-, 4’,5-dihydroxy- and 3’-hydroxy-4’-methoxy diclofenac. Diclofenac is eliminated through metabolism and subsequent urinary and biliary excretion of the glucuronide and the sulfate conjugates of the metabolites.

11. NONCLINICAL TOXICOLOGY

11.1 Carcinogenesis, Mutagenesis, Impairment of Fertility

Carcinogenesis

In dermal carcinogenicity study, daily external applications of diclofenac for two years did not increase neoplasm incidence. In a photocarcinogenicity study, external application of diclofenac resulted in an earlier median time of onset of tumors.

Mutagenesis

Diclofenac was not mutagenic or clastogenic in genotoxicity tests that included the bacterial reverse mutation assay, in vitro mouse lymphoma point mutation assay, chromosomal aberration studies in Chinese hamster ovarian cells in vitro, and in vivo rat chromosomal aberration assay of bone marrow cells.

Impairment of Fertility

Based on the mechanism of action, the use of prostaglandin-mediated NSAIDs, including diclofenac, may delay or prevent rupture of ovarian follicles, which ash been associated with reversible infertility in some women. Consider withdrawal of NSAIDs, including diclofenac, in women who have difficulties conceiving or who are undergoing investigation of infertility.

12. HOW SUPPLIED / STORAGE & HANDLING

12.1 How Supplied

Xiclo™ Transdermal Patch comes in a sealed pouch bag. Each patch is 2 in x 2 in (5.08 cm x 10.16 cm) and consists of an adhesive side containing the active/inactive ingredients and an outer surface backing layer. The adhesive side is covered with a removable, clear, unprinted, plastic film. The outer surface of the backing layer is imprinted with the Xiclo™ Transdermal Patch logo.

Xiclo™ Transdermal Patch is available as a unit box containing 10 patches (5 pouch bags). NDC 83295-5500-1

12.2 Storage

Store unit box between 69o-77o F (20o-25o C). Excursions between 15o-30o C (59o-86o F) are allowed. Keep Xiclo™ Transdermal Patch in the sealed pouch bags until immediately before use.

12.3 Handling and Disposal

Unintended exposure to diclofenac can cause irritation of the eyes, skin, respiratory tract, and mucous membranes. Avoid contact with your eyes, nose, or mouth. Keep used and unused patches out of the reach of children and pets. Pouch bags are not child resistant. Wash hands with soap and water after handling the patches. If irritation or a burning sensation occurs during application, remove the patch and do not reapply until the irritation subsides. After use, fold patches so that the adhesive sticks to itself, then safely discard used patches where children and pets cannot get to them.

13. PATIENT COUNSELING INFORMATION

- Inform patients that the treated area may be sensitive to heat (e.g., hot showers/bath, direct sunlight, vigorous exercise) for a few days following treatment.
- Instruct patients not to apply diclofenac external to open skin wounds, infections, inflammations, or exfoliative dermatitis, as it may affect absorption and reduce tolerability of the drug.
- Inform patients that as a result of treatment-related increases in pain, small transient increases in blood pressure may occur during and shortly after XiclofenTM Transdermal Patch treatment and that blood pressure will be monitored during the treatment process. If any cardiovascular event occurs, patients should notify a healthcare professional immediately.

14. GENERAL INFORMATION ON NSAIDs

- Medicines are sometimes prescribed for purposes other than those listed in a Medication Guide. Do not use NSAIDs for a condition for which it was not prescribed. Do not give NSAIDs to other people, even if they have the same symptoms that you have. It may harm them. You can ask your pharmacist or healthcare provider about more information on the effective use of NSAIDs to avoid adverse effects.

Manufactured for Strand Health Group, Las Vegas, NV 89102, USA.

Copyright © 2025 Strand Health Group, LLC. All Rights Reserved.

For comments or questions, please email cs@strandhealthgroup.com.

NDC 83295-5500-1

Xiclo™ Transdermal Patch

Rx Only

[Xiclo Patch Logo]